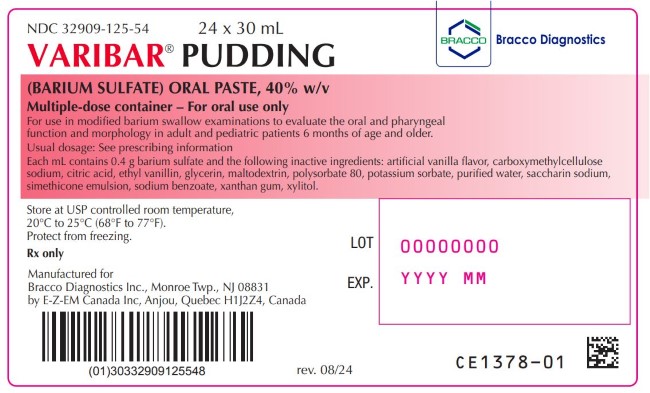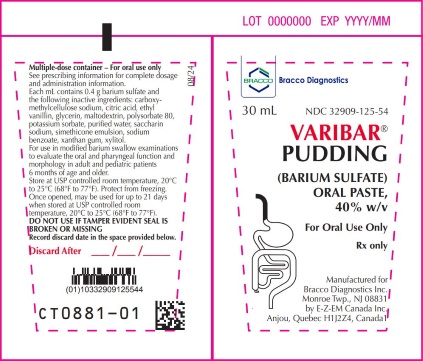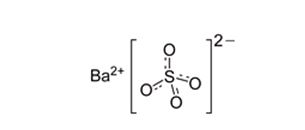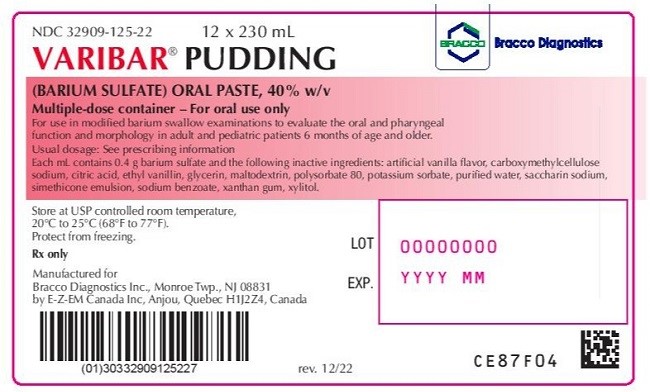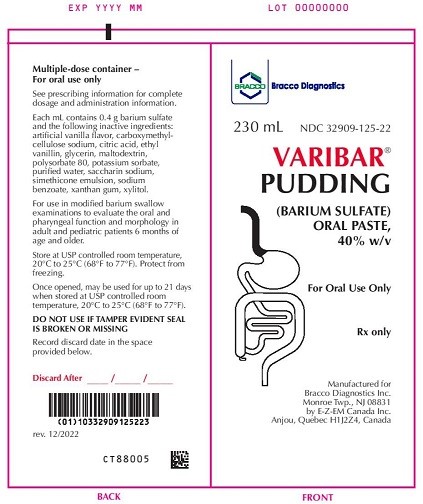 DRUG LABEL: Varibar Pudding
NDC: 32909-125 | Form: PASTE
Manufacturer: E-Z-EM Canada Inc
Category: prescription | Type: HUMAN PRESCRIPTION DRUG LABEL
Date: 20241106

ACTIVE INGREDIENTS: Barium Sulfate 400 mg/1 mL
INACTIVE INGREDIENTS: ANHYDROUS CITRIC ACID; CARBOXYMETHYLCELLULOSE SODIUM, UNSPECIFIED FORM; DIMETHICONE 350; DIMETHICONE 1000; ETHYL VANILLIN; GLYCERIN; MALTODEXTRIN; POLYSORBATE 80; POTASSIUM SORBATE; SACCHARIN SODIUM; SILICON DIOXIDE; SODIUM BENZOATE; WATER; XANTHAN GUM; XYLITOL

HIGHLIGHTS OF PRESCRIBING INFORMATION

These highlights do not include all the information needed to use VARIBAR PUDDING safely and effectively. See full prescribing information for VARIBAR PUDDING.
VARIBAR PUDDING (barium sulfate) oral paste
Initial U.S. Approval: 2016

1 INDICATIONS AND USAGE

VARIBAR PUDDING is a radiographic contrast agent indicated for use in modified barium swallow examinations to evaluate the oral and pharyngeal function and morphology in adult and pediatric patients 6 months of age and older (1)

2 DOSAGE AND ADMINISTRATION

- For oral use only – administered by syringe or spoon (2.1)
  - Adults: 5 mL
  - Pediatric patients: 1-3 mL
- Multiple doses may be administered
- Maximum cumulative dose : 30 mL

3 DOSAGE FORMS AND STRENGTHS

Oral paste: barium sulfate (40% w/v) in a 30 mL or 230 mL multiple dose tube for oral administration (3)

4 CONTRAINDICATIONS

VARIBAR PUDDING is contraindicated in patients with:

- Known or suspected perforation of the gastrointestinal (GI) tract (4)
- Conditions associated with high risk for GI perforation (4)
- Known obstruction of the GI tract (4)
- Patients with trachea-esophageal fistula (4)
- Known hypersensitivity to barium sulfate or any of the excipients of VARIBAR PUDDING (4)

5 WARNINGS AND PRECAUTIONS

- Hypersensitivity reactions: Emergency equipment and trained personnel should be immediately available (5.1)
- Intra-abdominal leakage: May occur with conditions which increase the risk for perforation such as – carcinomas, GI fistula, Inflammatory bowel disease, gastric or duodenal ulcer, appendicitis, diverticulitis, or severe stenosis or obstructing lesions of the GI tract (5.2)
- Obstruction: Patients should maintain adequate hydration in days following barium sulfate procedure to avoid obstruction or impaction by baroliths (5.3)
- Aspiration Pneumonitis: Aspiration may occur during the modified barium swallow examination, monitor the patient for aspiration (5.4)

6 ADVERSE REACTIONS

Common adverse reactions include nausea, vomiting, diarrhea and abdominal cramping (6)

To report SUSPECTED ADVERSE REACTIONS, contact Bracco Diagnostics at 1-800-257-5181 or FDA at 1-800-FDA-1088 or www.fda.gov/medwatch.

FULL PRESCRIBING INFORMATION

1 INDICATIONS AND USAGE

VARIBAR PUDDING is indicated for modified barium swallow examinations to evaluate the oral and pharyngeal function and morphology in adult and pediatric patients 6 months of age and older.

2 DOSAGE AND ADMINISTRATION

2.1 Recommended Dosing

- The recommended oral dose of VARIBAR PUDDING delivered by oral syringe or spoon:
  - Adults 5 mL
  - Pediatric patients 1-3 mL
- During a single modified barium swallow examination, multiple doses of VARIBAR PUDDING may be administered as appropriate, to assess the patient during multiple swallows and different radiographic views.
- The maximum cumulative dose is 30 mL oral.
- Once opened, write the discard after date on the immediate container label. Discard any unused product after 21 days.

2.2 Important Administration Instructions

- Advise patients to hydrate following the barium sulfate procedure.
- Advise patient at risk for constipation or delayed gastrointestinal transit to monitor for worsening of their condition after administration of barium sulfate and seek medical attention if worsening and advise using laxatives to enhance gastrointestinal transit.

3 DOSAGE FORMS AND STRENGTHS

Oral paste: barium sulfate (40% w/v) supplied in a multiple-dose white polyethylene tube as a ready-to-use paste for oral administration. Each tube contains either 30 mL or 230 mL of paste.

4 CONTRAINDICATIONS

VARIBAR PUDDING is contraindicated in patients with:

- known or suspected perforation of the gastrointestinal (GI) tract;
- known obstruction of the GI tract;
- high risk of GI perforation such as those with a recent GI perforation, acute GI hemorrhage or ischemia, toxic megacolon, severe ileus, post GI surgery or biopsy, acute GI injury or burn, or recent radiotherapy to the pelvis;
- high risk for aspiration such as those with known or suspected tracheo-esophageal fistula or obtundation;
- known hypersensitivity to barium sulfate or any of the excipients of VARIBAR PUDDING.

5 WARNINGS AND PRECAUTIONS

5.1 Hypersensitivity Reactions

Barium sulfate preparations contain a number of excipients, including natural and artificial flavors and may induce serious hypersensitivity reactions. The manifestations include: hypotension, bronchospasm and other respiratory impairments, and dermal reactions including rashes, urticaria, and itching. A history of bronchial asthma, atopy, food allergies, or a previous reaction to a contrast agent may increase the risk for hypersensitivity reactions. Emergency equipment and trained personnel should be immediately available for treatment of a hypersensitivity reaction.

5.2 Intra-abdominal Barium Leakage

Administration of VARIBAR PUDDING may result in leakage of barium from the GI tract in the presence of conditions and ailments that increase the risk of perforation such as known carcinomas, GI fistula, inflammatory bowel disease, gastric or duodenal ulcer, appendicitis, or diverticulitis, and in patients with a severe stenosis at any level of the gastrointestinal tract, especially if it is distal to the stomach. The barium leakage has been associated with peritonitis and granuloma formation. The use of VARIBAR PUDDING is contraindicated in patients at high risk of perforation of the GI tract [see Contraindications (4)].

5.3 Delayed Gastrointestinal Transit and Obstruction

Orally administered barium sulfate may accumulate proximal to a constricting lesion of the colon, causing obstruction or impaction with development of baroliths (inspissated barium associated with feces) and may lead to abdominal pain, appendicitis, bowel obstruction, or rarely perforation. Patients with the following conditions are at higher risk for developing obstruction or baroliths: severe stenosis at any level of the GI tract, with impaired gastrointestinal motility, electrolyte imbalance, dehydration, on a low residue diet, taking medications that delay GI motility, constipation, pediatric patients with cystic fibrosis or Hirschsprung disease, and the elderly. [see Use in Specific Populations (8.4, 8.5)]. To reduce the risk of delayed GI transit and obstruction, patients should maintain adequate hydration after the barium sulfate procedure and consider the administration of laxatives.

5.4 Aspiration Pneumonitis

Oral administration of barium is associated with aspiration pneumonitis, especially in patients with a history of food aspiration or with compromised swallowing mechanism. Vomiting following oral administration of barium sulfate may lead to aspiration pneumonitis. In patients at risk for aspiration, begin the procedure with a small ingested volume of VARIBAR PUDDING. The use of VARIBAR PUDDING is contraindicated in patients with trachea-esophageal fistula [see Contraindications (4)]. Monitor the patient closely for aspiration, discontinue administration of VARIBAR PUDDING if aspiration is suspected, and monitor for development of aspiration pneumonitis.

5.5 Systemic Embolization

Barium sulfate products may occasionally intravasate into the venous drainage of the large bowel and enter the circulation as a "barium embolus" leading to potentially fatal complications which include systemic and pulmonary embolism, disseminated intravascular coagulation, septicemia and prolonged severe hypotension. Although this complication is exceedingly uncommon after oral administration of a barium sulfate suspension, monitor patients for potential intravasation when administering barium sulfate.

6 ADVERSE REACTIONS

The following adverse reactions have been identified from spontaneous reporting or clinical studies of barium sulfate administered orally. Because the reactions are reported voluntarily from a population of uncertain size, it is not always possible to reliably estimate their frequency or to establish a causal relationship to drug exposure

- Nausea, vomiting, diarrhea and abdominal cramping
- Serious adverse reactions and fatalities include aspiration pneumonitis, barium sulfate impaction, intestinal perforation with consequent peritonitis and granuloma formation, vasovagal and syncopal episodes

8 USE IN SPECIFIC POPULATIONS

8.1 Pregnancy

Risk Summary

VARIBAR PUDDING is not absorbed systemically following oral administration, and maternal use is not expected to result in fetal exposure to the drug. [see Clinical Pharmacology (12.3)]

8.2 Lactation

Risk Summary

VARIBAR PUDDING is not absorbed systemically by the mother following oral administration and breastfeeding is not expected to result in exposure of the infant to the drug. [see Clinical Pharmacology (12.3)]

8.4 Pediatric Use

The efficacy of VARIBAR PUDDING in pediatric patients above 6 months of age is based on successful opacification of the pharynx during modified barium swallow examinations [see Clinical Pharmacology (12.1)]. Safety and dosing recommendations in pediatric patients above 6 months of age are based on clinical experience [see Indications (1), Dosage and Administration (2.1)].

VARIBAR PUDDING is contraindicated in pediatric patients with tracheo-esophageal fistula. [see Contraindications (4)]. Pediatric patients with a history of asthma or food allergies may be at increased risk for development of hypersensitivity reactions [see Warnings and Precautions (5.1)]. Pediatric patients with cystic fibrosis or Hirschsprung disease should be monitored for bowel obstruction after use [see Warnings and Precautions (5.3)].

8.5 Geriatric Use

Clinical studies of VARIBAR PUDDING did not include sufficient numbers of subjects aged 65 and over to determine whether they respond differently from younger subjects. Other reported clinical experience has not identified differences in responses between the elderly and younger patients. In general, dose selection for an elderly patient should be cautious, usually starting at the low end of the dosing range, reflecting the greater frequency of decreased hepatic, renal, or cardiac function, and of concomitant disease or other drug therapy

11 DESCRIPTION

VARIBAR PUDDING (barium sulfate) is a radiographic contrast agent that is supplied as a 40 % w/v ready to use paste with a vanilla aroma for oral administration. The active ingredient barium sulfate is designated chemically as BaSO4 with a molecular weight of 233.4 g/mol and the following chemical structure:

VARIBAR PUDDING has a viscosity of 5000 cPs and contains the following excipients: artificial vanilla flavor, carboxymethylcellulose sodium, citric acid, ethyl vanillin, glycerin, maltodextrin, polysorbate 80, potassium sorbate, purified water, saccharin sodium, simethicone emulsion, sodium benzoate, xanthan gum, and xylitol.

12 CLINICAL PHARMACOLOGY

12.1 Mechanism of Action

Due to its high atomic number, barium (the active ingredient in VARIBAR PUDDING) is opaque to x-rays and therefore acts as a positive contrast agent for radiographic studies.

12.2 Pharmacodynamics

Barium sulfate is biologically inert and has no known pharmacological effects.

12.3 Pharmacokinetics

Under physiological conditions, barium sulfate passes through the gastrointestinal tract in an unchanged form and is absorbed only in small, pharmacologically insignificant amounts.

13 NONCLINICAL TOXICOLOGY

13.1 Carcinogenesis, Mutagenesis, Impairment of Fertility

No animal studies have been performed to evaluate the carcinogenic potential of barium sulfate or potential effects on fertility.

16 HOW SUPPLIED/STORAGE AND HANDLING

VARIBAR PUDDING is supplied as a paste in a multiple-dose polyethylene tube containing either 30 mL or 230 mL of barium sulfate (40 % w/v).

Provided as: 24 X 30 mL tubes (NDC 32909-125-54); 12 X 230 mL tubes (NDC 32909-125-22)

Store at USP controlled room temperature 20°C to 25°C (68°F to 77°F). Protect from freezing.

Once opened, VARIBAR PUDDING may be used for up to 21 days when stored at USP controlled room temperature, 20°C to 25°C (68°F to 77°F).

17 PATIENT COUNSELING INFORMATION

After administration, advise patients to:

- Maintain adequate hydration.
- Seek medical attention for worsening of constipation or slow gastrointestinal passage.
- Seek medical attention for any delayed onset of hypersensitivity: rash, urticaria, or respiratory difficulty.

Rx only

Manufactured for
Bracco Diagnostics Inc.
Monroe Township, NJ 08831
by EZEM Canada Inc
Anjou (Quebec) Canada H1J 2Z4

VARIBAR® is a registered trademark of E-Z-EM, Inc.

Revised: August 2024
CL87D-04

230 mL Varibar Pudding Label

230 mL Varibar Pudding Tube

30 mL Varibar Pudding Label

30 mL Varibar Pudding Tube